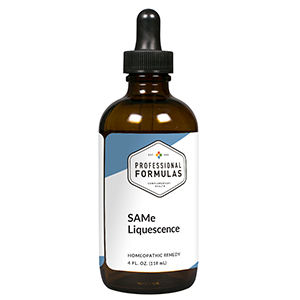 DRUG LABEL: SAMe Liquescence
NDC: 63083-3036 | Form: LIQUID
Manufacturer: Professional Complementary Health Formulas
Category: homeopathic | Type: HUMAN OTC DRUG LABEL
Date: 20190815

ACTIVE INGREDIENTS: PASSIFLORA INCARNATA FLOWERING TOP 1 [hp_X]/118 mL; ADEMETIONINE 3 [hp_X]/118 mL; METHIONINE 4 [hp_X]/118 mL; CYANOCOBALAMIN 4 [hp_X]/118 mL; ADENOSINE TRIPHOSPHATE 6 [hp_X]/118 mL; FOLIC ACID 6 [hp_X]/118 mL; HYPERICUM PERFORATUM WHOLE 6 [hp_X]/118 mL; PHOSPHATIDYLCHOLINE, SOYBEAN 6 [hp_X]/118 mL; PHOSPHATIDYL SERINE 6 [hp_X]/118 mL; NIACIN 6 [hp_X]/118 mL; PYRIDOXINE 6 [hp_X]/118 mL; BOS TAURUS LIMBIC SYSTEM 8 [hp_X]/118 mL; THIAMINE 8 [hp_X]/118 mL; CALCIUM LACTATE 9 [hp_X]/118 mL; ZINC GLUCONATE 9 [hp_X]/118 mL; GLUTATHIONE 12 [hp_X]/118 mL; FERROUS CATION 12 [hp_X]/118 mL; SEROTONIN 12 [hp_X]/118 mL; MAGNESIUM GLUCONATE 15 [hp_X]/118 mL; POTASSIUM GLUCONATE 15 [hp_X]/118 mL
INACTIVE INGREDIENTS: ALCOHOL; WATER

T36

ACTIVE INGREDIENTS

Passiflora incarnata 1X
SAMe 3X
Methionine 4X
Vitamin B12 4X
ATP 6X
Folic acid 6X
Hypericum perforatum 6X
Phosphatidylcholine 6X
Phosphatidylserine 6X
Vitamin B3 6X
Vitamin B6 6X
Limbic system 8X
Vitamin B1 8X
Calcium lactate 9X
Zinc gluconate 9X
Glutathione 12X
Iron gluconate 12X
Serotonin 12X
Magnesium gluconate 15X
Potassium gluconate 15X

QUESTIONS

Professional Formulas

PO Box 2034 Lake Oswego, OR 97035

INDICATIONS

For the temporary relief of sadness, anxiousness, mild muscle or joint pain, stiffness, or inflammation, occasional headache, or fatigue.*

PURPOSE

*Claims based on traditional homeopathic practice, not accepted medical evidence. Not FDA evaluated.

WARNINGS

Consult a doctor if condition worsens or if symptoms persist. Keep out of the reach of children. In case of overdose, get medical help or contact a poison control center right away. If pregnant or breastfeeding, ask a healthcare professional before use.

Keep out of the reach of children.

PREGNANCY OR BREAST FEEDING

If pregnant or breastfeeding, ask a healthcare professional before use.

DIRECTIONS

Place drops under tongue 30 minutes before/after meals. Adults and children 12 years and over: Take one full dropper up to 2 times per day. Consult a physician for use in children under 12 years of age.

OTHER INFORMATION

Tamper resistant. If seal is broken, do not use. After opening, close container tightly and store at room temperature away from heat.

INACTIVE INGREDIENTS

20% ethanol, purified water.

LABEL

Est 1985

Professional Formulas

Complementary Health

SAMe Liquescence

Homeopathic Remedy

4 FL. OZ. (118 mL)